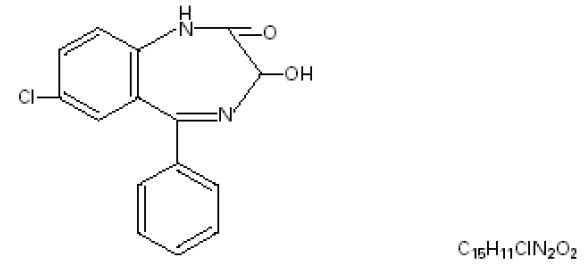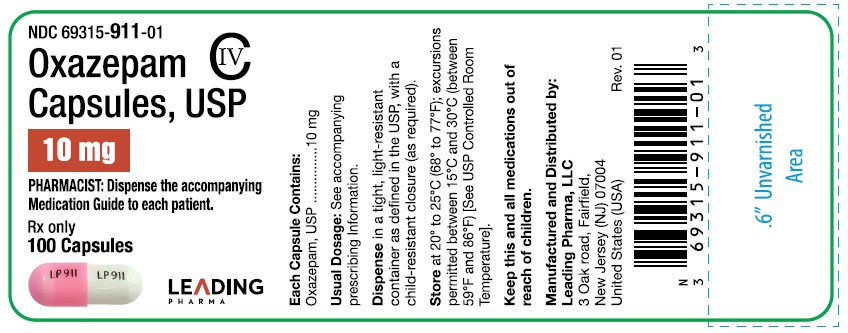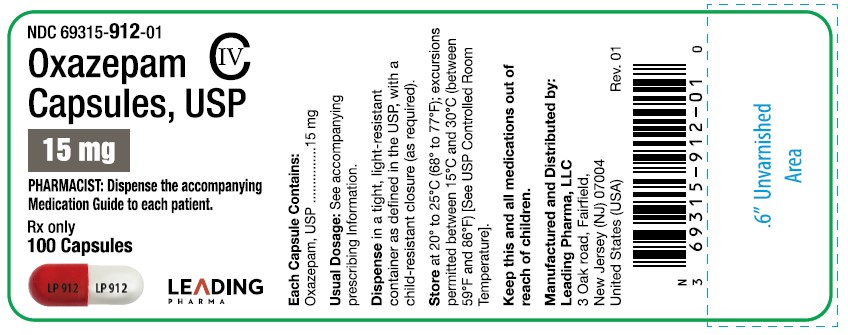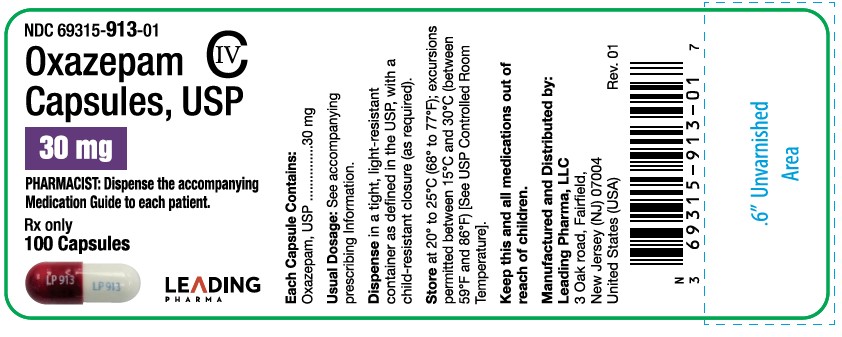 DRUG LABEL: OXAZEPAM
NDC: 69315-911 | Form: CAPSULE
Manufacturer: Leading Pharma, LLC
Category: prescription | Type: Human Prescription Drug Label
Date: 20250711
DEA Schedule: CIV

ACTIVE INGREDIENTS: OXAZEPAM 10 mg/1 1
INACTIVE INGREDIENTS: LACTOSE MONOHYDRATE; STARCH, CORN; CROSCARMELLOSE SODIUM; HYPROMELLOSE, UNSPECIFIED; SODIUM LAURYL SULFATE; MAGNESIUM STEARATE; GELATIN; TITANIUM DIOXIDE; D&C RED NO. 28; FD&C RED NO. 40; FERROSOFERRIC OXIDE; AMMONIA; POTASSIUM HYDROXIDE; PROPYLENE GLYCOL; WATER; FD&C BLUE NO. 2 ALUMINUM LAKE; SHELLAC

Oxazepam Capsules, USP
C-IV

BOXED WARNING

WARNING: RISKS FROM CONCOMITANT USE WITH OPIOIDS; ABUSE, MISUSE, AND ADDICTION; and DEPENDENCE AND WITHDRAWAL REACTIONS

- Concomitant use of benzodiazepines and opioids may result in profound sedation, respiratory depression, coma, and death.
- Reserve concomitant prescribing of these drugs for use in patients for whom alternative treatment options are inadequate.
- Limit dosages and durations to the minimum required.
- Follow patients for signs and symptoms of respiratory depression and sedation [see WARNINGSand PRECAUTIONS].
- The use of benzodiazepines, including oxazepam, exposes users to risks of abuse, misuse, and addiction, which can lead to overdose or death. Abuse and misuse of benzodiazepines commonly involve concomitant use of other medications, alcohol, and/or illicit substances, which is associated with an increased frequency of serious adverse outcomes. Before prescribing oxazepam and throughout treatment, assess each patient’s risk for abuse, misuse, and addiction [see WARNINGS].
- The continued use of benzodiazepines, including oxazepam, may lead to clinically significant physical dependence. The risks of dependence and withdrawal increase with longer treatment duration and higher daily dose. Abrupt discontinuation or rapid dosage reduction of oxazepam after continued use may precipitate acute withdrawal reactions, which can be life-threatening. To reduce the risk of withdrawal reactions, use a gradual taper to discontinue oxazepam or reduce the dosage [see DOSAGE AND ADMINISTRATIONand WARNINGS].

Description

Oxazepam, USP is the first of a chemical series of compounds known as the 3-hydroxybenzodiazepinones.

A therapeutic agent providing versatility and flexibility in control of common emotional disturbances, this product exerts prompt action in a wide variety of disorders associated with anxiety, tension, agitation, and irritability, and anxiety associated with depression. In tolerance and toxicity studies on several animal species, this product reveals significantly greater safety factors than related compounds (chlordiazepoxide and diazepam) and manifests a wide separation of effective doses and doses inducing side effects.

Oxazepam capsule, USP contains 10 mg, 15 mg, or 30 mg oxazepam, USP. The following inactive ingredients are contained in these capsules: lactose monohydrate, pregelatinized starch, croscarmellose sodium, hypromellose, sodium lauryl sulfate, and magnesium stearate. The capsule shell contains gelatin and titanium dioxide. The 10 mg capsule also contains: D&C Red #28 and FD&C Red #40, the 15 mg capsule also contains: FD&C Red #40 and D&C Yellow #10 and the 30 mg capsule also contains: D&C Red #28, FD&C Red #40 and FD&C Blue #1. The imprinting ink contains strong ammonia solution, black iron oxide, potassium hydroxide, propylene glycol, purified water, titanium dioxide, FD&C Blue #2 aluminum lake and shellac.

Oxazepam, USP is 7-chloro-1,3-dihydro-3-hydroxy-5-phenyl-2H-1,4-benzodiazepin-2-one. A white crystalline powder with a molecular weight of 286.7, its structural formula is as follows:

CLINICAL PHARMACOLOGY

Pharmacokinetic testing in 12 volunteers demonstrated that a single 30 mg dose of a capsule, tablet or suspension will result in an equivalent extent of absorption. For the capsule and tablet, peak plasma levels averaged 450 mg/mL and were observed to occur about 3 hours after dosing. The mean elimination half-life for oxazepam was approximately 8.2 hours (range 5.7 to 10.9 hours).

This product has a single, major inactive metabolite in man, a glucuronide excreted in the urine.

Age (less than 80 years old) does not appear to have a clinically significant effect on oxazepam kinetics. A statistically significant increase in elimination half-life in the very elderly (greater than 80 years of age) as compared to younger subjects has been reported, due to a 30% increase in volume of distribution, as well as a 50% reduction in unbound clearance of oxazepam in the very elderly [See PRECAUTIONS, Geriatric Use].

INDICATIONS

Oxazepam capsules are indicated for the management of anxiety disorders or for the short-term relief of the symptoms of anxiety. Anxiety or tension associated with the stress of everyday life usually does not require treatment with an anxiolytic.

Anxiety associated with depression is also responsive to oxazepam therapy.

This product has been found particularly useful in the management of anxiety, tension, agitation and irritability in older patients.

Alcoholics with acute tremulousness, inebriation, or with anxiety associated with alcohol withdrawal are responsive to therapy.

The effectiveness of oxazepam in long-term use, that is, more than 4 months, has not been assessed by systematic clinical studies. The physician should periodically reassess the usefulness of the drug for the individual patient.

CONTRAINDICATIONS

History of previous hypersensitivity reaction to oxazepam. Oxazepam is not Indicated in psychoses.

WARNINGS

Risks from Concomitant Use with Opioids: Concomitant use of benzodiazepines, including oxazepam, and opioids may result in profound sedation, respiratory depression, coma, and death. Because of these risks, reserve concomitant prescribing of these drugs in patients for whom alternative treatment options are inadequate.

Observational studies have demonstrated that concomitant use of opioid analgesics and benzodiazepines increases the risk of drug-related mortality compared to use of opioids alone. If a decision is made to prescribe oxazepam concomitantly with opioids, prescribe the lowest effective dosages and minimum durations of concomitant use, and follow patients closely for signs and symptoms of respiratory depression and sedation. In patients already receiving an opioid analgesic, prescribe a lower initial dose of oxazepam than indicated in the absence of an opioid and titrate based on clinical response. If an opioid is initiated in a patient already taking oxazepam, prescribe a lower initial dose of the opioid and titrate based upon clinical response.

Advise both patients and caregivers about the risks of respiratory depression and sedation when oxazepam is used with opioids. Advise patients not to drive or operate heavy machinery until the effects of concomitant use with the opioid have been determined [see PRECAUTIONS: Drug Interactions].

Abuse, Misuse, and Addiction: The use of benzodiazepines, including oxazepam, exposes users to the risks of abuse, misuse, and addiction, which can lead to overdose or death. Abuse and misuse of benzodiazepines often (but not always) involve the use of doses greater than the maximum recommended dosage and commonly involve concomitant use of other medications, alcohol, and/or illicit substances, which is associated with an increased frequency of serious adverse outcomes, including respiratory depression, overdose, or death [see DRUG ABUSE AND DEPENDENCE: Abuse].

Before prescribing oxazepam and throughout treatment, assess each patient’s risk for abuse, misuse, and addiction (e.g., using a standardized screening tool). Use of oxazepam, particularly in patients at elevated risk, necessitates counseling about the risks and proper use of oxazepam along with monitoring for signs and symptoms of abuse, misuse, and addiction. Prescribe the lowest effective dosage; avoid or minimize concomitant use of CNS depressants and other substances associated with abuse, misuse, and addiction (e.g., opioid analgesics, stimulants); and advise patients on the proper disposal of unused drug. If a substance use disorder is suspected, evaluate the patient and institute (or refer them for) early treatment, as appropriate.

Dependence and Withdrawal Reactions: To reduce the risk of withdrawal reactions, use a gradual taper to discontinue oxazepam or reduce the dosage (a patient-specific plan should be used to taper the dose) [see DOSAGE AND ADMINISTRATION: Discontinuation or Dosage Reduction of Oxazepam].

Patients at an increased risk of withdrawal adverse reactions after benzodiazepine discontinuation or rapid dosage reduction include those who take higher dosages, and those who have had longer durations of use.

Acute Withdrawal Reactions

The continued use of benzodiazepines, including oxazepam, may lead to clinically significant physical dependence. Abrupt discontinuation or rapid dosage reduction of oxazepam after continued use, or administration of flumazenil (a benzodiazepine antagonist) may precipitate acute withdrawal reactions, which can be life-threatening (e.g., seizures) [see DRUG ABUSE AND DEPENDENCE: Dependence].

Protracted Withdrawal Syndrome

In some cases, benzodiazepine users have developed a protracted withdrawal syndrome with withdrawal symptoms lasting weeks to more than 12 months [see DRUG ABUSE AND DEPENDENCE: Dependence].

As with other CNS-acting drugs, patients should be cautioned against driving automobiles or operating dangerous machinery until it is known that they do not become drowsy or dizzy on oxazepam therapy.

Patients should be warned that the effects of alcohol or other CNS-depressant drugs may be additive to those of Oxazepam, possibly requiring adjustment of dosage or elimination of such agents.

Neonatal Sedation and Withdrawal Syndrome

Use of oxazepam late in pregnancy can result in sedation (respiratory depression, lethargy, hypotonia) and/or withdrawal symptoms (hyperreflexia, irritability, restlessness, tremors, inconsolable crying, and feeding difficulties) in the neonate (see PRECAUTIONS, Pregnancy). Monitor neonates exposed to oxazepam during pregnancy or labor for signs of sedation and monitor neonates exposed to oxazepam during pregnancy for signs of withdrawal; manage these neonates accordingly.

PRECAUTIONS

General

Although hypotension has occurred only rarely, oxazepam should be administered with caution to patients in whom a drop in blood pressure might lead to cardiac complications. This is particularly true in the elderly patient.

Information for Patients

Advise the patient to read the FDA-approved patient labeling (Medication Guide).

Risks from Concomitant Use with Opioids

Advise both patients and caregivers about the risks of potentially fatal respiratory depression and sedation when oxazepam is used with opioids and not to use such drugs concomitantly unless supervised by a health care provider. Advise patients not to drive or operate heavy machinery until the effects of concomitant use with the opioid have been determined [see WARNINGS: Risks from Concomitant Use with Opioids and PRECAUTIONS: Drug Interactions].

Abuse, Misuse, and Addiction

Inform patients that the use of oxazepam, even at recommended dosages, exposes users to risks of abuse, misuse, and addiction, which can lead to overdose and death, especially when used in combination with other medications (e.g., opioid analgesics), alcohol, and/or illicit substances. Inform patients about the signs and symptoms of benzodiazepine abuse, misuse, and addiction; to seek medical help if they develop these signs and/or symptoms; and on the proper disposal of unused drug [see WARNINGS: Abuse, Misuse, and Addictionand DRUG ABUSE AND DEPENDENCE].

Withdrawal Reactions

Inform patients that the continued use of oxazepam may lead to clinically significant physical dependence and that abrupt discontinuation or rapid dosage reduction of oxazepam may precipitate acute withdrawal reactions, which can be life-threatening. Inform patients that in some cases, patients taking benzodiazepines have developed a protracted withdrawal syndrome with withdrawal symptoms lasting weeks to more than 12 months. Instruct patients that discontinuation or dosage reduction of oxazepam may require a slow taper [see WARNINGS: Dependence and Withdrawal ReactionsandDRUG ABUSE AND DEPENDENCE].

Pregnancy

Advise pregnant females that use of oxazepam late in pregnancy can result in sedation (respiratory depression, lethargy, hypotonia) and/or withdrawal symptoms (hyperreflexia, irritability, restlessness, tremors, inconsolable crying, and feeding difficulties) in newborns (see Warnings, Neonatal Sedation and Withdrawal Syndromeand Precautions, Pregnancy). Instruct patients to inform their healthcare provider if they are pregnant.

Nursing

Instruct patients to notify their healthcare provider if they are breastfeeding or intend to breastfeed. Instruct breastfeeding patients using oxazepam to monitor infants for excessive sedation, poor feeding and poor weight gain, and to seek medical attention if they notice these signs (see Precautions, Nursing Mothers).

Drug Interactions

The concomitant use of benzodiazepines and opioids increases the risk of respiratory depression because of actions at different receptor sites in the CNS that control respiration. Benzodiazepines interact at GABAA sites and opioids interact primarily at mu receptors. When benzodiazepines and opioids are combined, the potential for benzodiazepines to significantly worsen opioid-related respiratory depression exists. Limit dosage and duration of concomitant use of benzodiazepines and opioids and monitor patients closely for respiratory depression and sedation.

Pregnancy

Risk Summary

Neonates born to mothers using benzodiazepines late in pregnancy have been reported to experience symptoms of sedation and/or neonatal withdrawal (see WARNINGS, Neonatal Sedation and Withdrawal Syndromeand PRECAUTIONS: Clinical Considerations). Available data from published observational studies of pregnant women exposed to benzodiazepines do not report a clear association with benzodiazepines and major birth defects (see Data).

The estimated background risk of major birth defects and miscarriage for the indicated population is unknown. All pregnancies have a background risk of birth defect, loss, or other adverse outcomes. In the U.S. general population, the estimated risk of major birth defects and of miscarriage in clinically recognized pregnancies is 2% to 4% and 15% to 20%, respectively.

Clinical Considerations

Fetal/Neonatal Adverse Reactions

Benzodiazepines cross the placenta and may produce respiratory depression, hypotonia and sedation in neonates. Monitor neonates exposed to oxazepam during pregnancy or labor for signs of sedation, respiratory depression, hypotonia, and feeding problems. Monitor neonates exposed to oxazepam during pregnancy for signs of withdrawal. Manage these neonates accordingly (see WARNINGS, Neonatal Sedation and Withdrawal Syndrome).

Data

Human Data

Published data from observational studies on the use of benzodiazepines during pregnancy do not report a clear association with benzodiazepines and major birth defects. Although early studies reported an increased risk of congenital malformations with diazepam and chlordiazepoxide, there was no consistent pattern noted. In addition, the majority of more recent case-control and cohort studies of benzodiazepine use during pregnancy, which were adjusted for confounding exposures to alcohol, tobacco and other medications, have not confirmed these findings.

Animal Data

Reproductive studies in animals were performed in mice, rats, and two strains of rabbits. Occasional anomalies (reduction of tarsals, tibia, metatarsals, malrotated limbs, gastroschisis, malformed skull, and microphthalmia) were seen in drug-treated rabbits without relationship to dosage. Although all of these anomalies were not present in the concurrent control group, they have been reported to occur randomly in historical controls. At doses of 40 mg/kg and higher, there was evidence of fetal resorption and increased fetal loss in rabbits which was not seen at lower doses.

Nursing Mothers

Risk Summary

Oxazepam is present in breast milk. There are reports of sedation, poor feeding and poor weight gain in infants exposed to benzodiazepines through breast milk (see Clinical Considerations). The effects of oxazepam on milk production are unknown. The developmental and health benefits of breastfeeding should be considered along with the mother’s clinical need for oxazepam and any potential adverse effects on the breastfed infant from oxazepam or from the underlying maternal condition.

Clinical Considerations

Infants exposed to oxazepam through breast milk should be monitored for sedation, poor feeding and poor weight gain.

Pediatric Use

Safety and effectiveness in pediatric patients under 6 years of age have not been established. Absolute dosage for pediatric patients 6 to 12 years of age is not established.

Geriatric Use

Clinical studies of oxazepam were not adequate to determine whether subjects aged 65 and over respond differently than younger subjects. Age (less than 80 years old) does not appear to have a clinically significant effect on oxazepam kinetics [seeCLINICAL PHARMACOLOGY].

Clinical circumstances, some of which may be more common in the elderly, such as hepatic or renal impairment, should be considered. Greater sensitivity of some older individuals to the effects of oxazepam (e.g., sedation, hypotension, paradoxical excitation) cannot be ruled out [see PRECAUTIONS, General and ADVERSE REACTIONS]. In general, dose selection for oxazepam for elderly patients should be cautious, usually starting at the lower end of the dosing range [see DOSAGE AND ADMNSTRATION].

ADVERSE REACTIONS

The necessity for discontinuation of therapy due to undesirable effects has been rare. Transient mild drowsiness is commonly seen in the first few days of therapy. If it persists, the dosage should be reduced. In few instances, dizziness, vertigo, headache and rarely syncope have occurred either alone or together with drowsiness. Mild paradoxical reactions: i.e., excitement, stimulation of affect, have been reported in psychiatric patients; these reactions may be secondary to relief of anxiety and usually appear in the first two weeks of therapy.

Other side effects occurring during oxazepam therapy include rare instances of minor diffuse skin rashes - morbilliform, urticarial, and maculopapular, nausea, lethargy, edema, slurred speech, tremor, and altered libido. Such side effects have been infrequent and are generally controlled with reduction of dosage. A case of an extensive fixed drug eruption also has been reported.

Although rare, leukopenia and hepatic dysfunction including jaundice have been reported during therapy. Periodic blood counts and liver-function tests are advisable. Ataxia with oxazepam has been reported in rare instances and does not appear to be specifically related to dose or age.

Although the following side reactions have not as yet been reported with oxazepam, they have occurred with related compounds (chlordiazepoxide and diazepam): paradoxical excitation with severe rage reactions, hallucinations, menstrual irregularities, change in EEG pattern, blood dyscrasias including agranulocytosis, blurred vision, diplopia, incontinence, stupor, disorientation, fever and euphoria.

Transient amnesia or memory impairment has been reported in association with the use of benzodiazepines.

To report SUSPECTED ADVERSE REACTIONS, contact Leading Pharma, LLC at 1-844-740-7500 or FDA at 1-800-FDA-1088 or “http://www.fda.gov/medwatch" for voluntary reporting of adverse reactions.

DRUG ABUSE AND DEPENDENCE

Controlled Substance

Oxazepam is a schedule IV-controlled substance.

Abuse

Oxazepam is a benzodiazepine and a CNS depressant with a potential for abuse and addiction. Abuse is the intentional, nontherapeutic use of a drug, even once, for its desirable psychological or physiological effects. Misuse is the intentional use, for therapeutic purposes, of a drug by an individual in a way other than prescribed by a health care provider or for whom it was not prescribed. Drug addiction is a cluster of behavioral, cognitive, and physiological phenomena that may include a strong desire to take the drug, difficulties in controlling drug use (e.g., continuing drug use despite harmful consequences, giving a higher priority to drug use than other activities and obligations), and possible tolerance or physical dependence. Even taking benzodiazepines as prescribed may put patients at risk for abuse and misuse of their medication. Abuse and misuse may lead to addiction.

Abuse and misuse of benzodiazepines often (but not always) involve the use of doses greater than the maximum recommended dosage and commonly involve concomitant use of other medications, alcohol, and/or illicit substances, which is associated with an increased frequency of serious adverse outcomes, including respiratory depression, overdose, or death. Benzodiazepines are often sought by individuals who abuse drugs and other substances, and by individuals with addictive disorders [see WARNINGS: Abuse, Misuse, and Addiction].

The following adverse reactions have occurred with benzodiazepine abuse and/or misuse: abdominal pain, amnesia, anorexia, anxiety, aggression, ataxia, blurred vision, confusion, depression, disinhibition, disorientation, dizziness, euphoria, impaired concentration and memory, indigestion, irritability, muscle pain, slurred speech, tremors, and vertigo.

The following severe adverse reactions have occurred with benzodiazepine abuse and/or misuse: delirium, paranoia, suicidal ideation and behavior, seizures, coma, breathing difficulty, and death. Death is more often associated with polysubstance use (especially benzodiazepines with other CNS depressants such as opioids and alcohol).

Dependence

Physical Dependence

Oxazepam may produce physical dependence from continued therapy. Physical dependence is a state that develops as a result of physiological adaptation in response to repeated drug use, manifested by withdrawal signs and symptoms after abrupt discontinuation or a significant dose reduction of a drug. Abrupt discontinuation or rapid dosage reduction of benzodiazepines or administration of flumazenil, a benzodiazepine antagonist, may precipitate acute withdrawal reactions, including seizures, which can be life-threatening. Patients at an increased risk of withdrawal adverse reactions after benzodiazepine discontinuation or rapid dosage reduction include those who take higher dosages (i.e., higher and/or more frequent doses) and those who have had longer durations of use [see WARNINGS: Dependence and Withdrawal Reactions].

To reduce the risk of withdrawal reactions, use a gradual taper to discontinue oxazepam or reduce the dosage [see DOSAGE AND ADMINISTRATION: Discontinuation or Dosage Reduction of OxazepamandWARNINGS: Dependence and Withdrawal Reactions].

Acute Withdrawal Signs and Symptoms

Acute withdrawal signs and symptoms associated with benzodiazepines have included abnormal involuntary movements, anxiety, blurred vision, depersonalization, depression, derealization, dizziness, fatigue, gastrointestinal adverse reactions (e.g., nausea, vomiting, diarrhea, weight loss, decreased appetite), headache, hyperacusis, hypertension, irritability, insomnia, memory impairment, muscle pain and stiffness, panic attacks, photophobia, restlessness, tachycardia, and tremor. More severe acute withdrawal signs and symptoms, including life-threatening reactions, have included catatonia, convulsions, delirium tremens, depression, hallucinations, mania, psychosis, seizures, and suicidality.

Protracted Withdrawal Syndrome

Protracted withdrawal syndrome associated with benzodiazepines is characterized by anxiety, cognitive impairment, depression, insomnia, formication, motor symptoms (e.g., weakness, tremor, muscle twitches), paresthesia, and tinnitus that persists beyond 4 to 6 weeks after initial benzodiazepine withdrawal. Protracted withdrawal symptoms may last weeks to more than 12 months. As a result, there may be difficulty in differentiating withdrawal symptoms from potential re-emergence or continuation of symptoms for which the benzodiazepine was being used.

Tolerance

Tolerance to oxazepam may develop from continued therapy. Tolerance is a physiological state characterized by a reduced response to a drug after repeated administration (i.e., a higher dose of a drug is required to produce the same effect that was once obtained at a lower dose). Tolerance to the therapeutic effect of oxazepam may develop; however, little tolerance develops to the amnestic reactions and other cognitive impairments caused by benzodiazepines.

OVERDOSAGE

Overdosage of benzodiazepines is characterized by central nervous system depression ranging from drowsiness to coma. In mild to moderate cases, symptoms can include drowsiness, confusion, dysarthria, lethargy, hypnotic state, diminished reflexes, ataxia, and hypotonia. Rarely, paradoxical or disinhibitory reactions (including agitation, irritability, impulsivity, violent behavior, confusion, restlessness, excitement, and talkativeness) may occur. In severe overdosage cases, patients may develop respiratory depression and coma. Overdosage of benzodiazepines in combination with other CNS depressants (including alcohol and opioids) may be fatal (see WARNINGS, Abuse, Misuse, and Addiction). Markedly abnormal (lowered or elevated) blood pressure, heart rate, or respiratory rate raise the concern that additional drugs and/or alcohol are involved in the overdosage.

In managing benzodiazepine overdosage, employ general supportive measures, including intravenous fluids and airway management. Flumazenil, a specific benzodiazepine receptor antagonist indicated for the complete or partial reversal of the sedative effects of benzodiazepines in the management of benzodiazepine overdosage, can lead to withdrawal and adverse reactions, including seizures, particularly in the context of mixed overdosage with drugs that increase seizure risk (e.g., tricyclic and tetracyclic antidepressants) and in patients with long-term benzodiazepine use and physical dependency. The risk of withdrawal seizures with flumazenil use may be increased in patients with epilepsy. Flumazenil is contraindicated in patients who have received a benzodiazepine for control of a potentially life-threatening condition (e.g., status epilepticus). If the decision is made to use flumazenil, it should be used as an adjunct to, not as a substitute for, supportive management of benzodiazepine overdosage. See the flumazenil injection Prescribing Information.

Consider contacting a poison center (1-800-222-1222), poisoncontrol.org, or a medical toxicologist for additional overdosage management recommendations.

DOSAGE AND ADMINISTRATION

Because of the flexiblllty of this product and the range of emotional disturbances responsive to it, dosage should be individualized for maximum beneflcial effects.

Oxazepam | Usual Dose
Mild-to-moderate anxiety, with associated tension, itritability, agitation, or related symptoms of functional origin or seconday to organic disease. | 10 to 15 mg, 3 or 4 times daily
Severe anxiety syndromes, agitation, or anxiety associated with depression. | 15 to 30 mg, 3 or 4 times daily
Older patients with anxiety, tension, irritabillly, and agitation. | Initial dosage: 10 mg, 3 times daily. If necessary, increase cautiously to 15 mg, 3 or 4 times daily.
Alcoholics with acute inebriation, tremulousness, or anxiety on withdrawal. | 15 to 30 mg, 3 or 4 times daily

This product is not indicated in pediatric patients under 6 years of age. Absolute dosage tor pediatric patients 6 to 12 years of age is not established.

Discontinuation or Dosage Reduction of Oxazepam

To reduce the risk of withdrawal reactions, use a gradual taper to discontinue oxazepam or reduce the dosage. If a patient develops withdrawal reactions, consider pausing the taper or increasing the dosage to the previous tapered dosage level. Subsequently decrease the dosage more slowly [see WARNINGS: Dependence and Withdrawal Reactions and DRUG ABUSE AND DEPENDENCE: Dependence]

HOW SUPPLIED

Oxazepam capsules, USP are available as follows:

Oxazepam capsules, USP, 10 mg are almost white powder in a hard gelatin capsules with opaque pink and opaque white capsule, imprinted with "LP 911" in black ink on both cap and body. They are supplied as follows: NDC 69315-911-01 bottles of 100.

Oxazepam capsules, USP, 15 mg are almost white powder in a hard gelatin capsules with opaque red and opaque white capsule, imprinted with "LP 912" in black ink on both cap and body. They are supplied as follows: NDC 69315-912-01 bottles of 100.

Oxazepam capsules, USP, 30 mg are almost white powder in a hard gelatin capsules with opaque maroon and opaque white capsule, imprinted with "LP 913" in blue ink on both cap and body. They are supplied as follows: NDC 69315-913-01 bottles of 100.

Store at 20° to 25°C (68° to 77°F); excursions permitted between 15°C and 30°C (between 59°F and 86°F) [See USP Controlled Room Temperature].

Dispense in a tight, light-resistant container as defined in the USP, with a child-resistant closure (as required).

ANIMAL PHARMACOLOGY AND TOXICOLOGY

In mice, oxazepam exerts an anticonvulsant (anti-pentylenetetrazol) activity at 50-percent-effective doses of about 0.6 mg/kg orally. (Such anticonvulsant activity of benzodiazepines correlates with their tranquilizing properties.) To produce ataxia (rotabar test) and sedation (abolition of spontaneous motor activity), the 50-percent-effective doses of this product are greater than 5 mg/kg orally. Thus, about ten times the therapeutic (anticonvulsant) dose must be given before ataxia ensues, indicating a wide separation of effective doses and doses inducing side effects.

In evaluation of antianxiety activity of compounds, conflict behavioral tests in rats differentiate continuous response for food in the presence of anxiety-provoking stress (shock) from drug-induced motor incoordination. This product shows significant separation of doses required to relieve anxiety and doses producing sedation or ataxia. Ataxia-producing doses exceed those of related CNS-acting drugs.

Acute oral LD50 in mice is greater than 5000 mg/kg, compared to 800 mg/kg for a related compound (chlordiazepoxide).

Subacute toxicity studies in dogs for four weeks at 480 mg/kg daily showed no specific changes; at 960 mg/kg, two out of eight died with evidence of circulatory collapse. This wide margin of safety is significant compared to chlordiazepoxide HCl, which showed nonspecific changes in six dogs at 80 mg/kg. On chlordiazepoxide, two out of six died with evidence of circulatory collapse at 127 mg/kg, and six out of six died at 200 mg/kg daily. Chronic toxicity studies of oxazepam in dogs at 120 mg/kg/day for 52 weeks produced no toxic manifestation.

Fatty metamorphosis of the liver has been noted in six-week toxicity studies in rats given this product at 0.5% of the diet. Such accumulations of fat are considered reversible, as there is no liver necrosis or fibrosis. Breeding studies in rats through two successive litters did not produce fetal abnormality.

Oxazepam has not been adequately evaluated for mutagenic activity.

In a carcinogenicity study, oxazepam was administered with diet to rats for two years. Male rats receiving 30 times the maximum human dose showed a statistical increase, when compared to controls, in benign thyroid follicular cell tumors, testicular interstitial cell adenomas, and prostatic adenomas. An earlier published study reported that mice fed dietary dosages of 35 or 100 times the human daily dose of oxazepam for 9 months developed a dose-related increase in liver adenomas.1 In an independent analysis of some of the microscopic slides from this mouse study, several of these tumors were classified as liver carcinomas. At this time, there is no evidence that clinical use of oxazepam is associated with tumors.

REFERENCE

1. FOX, K.A, LAHCEN, R.B.: Liver-cell Adenomas and Peliosis Hepatis in Mice Associated with Oxazepam. Res. Commun. Chem. Pathol. Pharmacol. 8:481-488, 1974.

Manufactured and Distributed by:

Leading Pharma, LLC
3 Oak road, Fairfield,
New Jersey (NJ) 07004
United States (USA)

Rev.02, 06/24

PATIENT INFORMATION

MEDICATION GUIDE

Oxazepam (ox az' e pam) Capsules, USP C-IV

What is the most important information I should know about oxazepam?

- Oxazepam is a benzodiazepine medicine. Taking benzodiazepines with opioid medicines, alcohol, or other central nervous system (CNS) depressants (including street drugs) can cause severe drowsiness, breathing problems (respiratory depression), coma and death. Get emergency help right away if any of the following happens:
  - shallow or slowed breathing.
  - breathing stops (which may lead to the heart stopping)
  - excessive sleepiness (sedation).

Do not drive or operate heavy machinery until you know how taking oxazepam with opioids affects you.

Risk of abuse, misuse, and addiction. There is a risk of abuse, misuse, and addiction with benzodiazepines, including oxazepam, which can lead to overdose and serious side effects including coma and death.

- Serious side effects including coma and death have happened in people who have abused or misused benzodiazepines, including oxazepam. These serious side effects may also include delirium, paranoia, suicidal thoughts or actions, seizures, and difficulty breathing. Call your healthcare provider or go to the nearest hospital emergency room right away if you get any of these serious side effects.
- You can develop an addiction even if you take oxazepam exactly as prescribed by your healthcare provider.
- Take oxazepam exactly as your healthcare provider prescribed.
- Do not share your oxazepam with other people.
- Keep oxazepam in a safe place and away from children.

- Physical dependence and withdrawal reactions. Oxazepam can cause physical dependence and withdrawal reactions, especially if you continue to take oxazepam for several days to several weeks.
  - Do not suddenly stop taking oxazepam. Stopping oxazepam suddenly can cause serious and life-threatening side effects, including unusual movements, responses, or expressions, seizures, sudden and severe mental or nervous system changes, depression, seeing or hearing things that others do not see or hear an extreme increase in activity or talking, losing touch with reality, and suicidal thoughts or actions. Call your healthcare provider or go to the nearest hospital emergency room right away if you get any of these symptoms.
  - Some people who suddenly stop benzodiazepines have symptoms that can last for several weeks to more than 12 months, including, anxiety, trouble remembering, learning, or concentrating, depression, problems sleeping, feeling like insects are crawling under your skin, weakness, shaking, muscle twitching, burning or prickling feeling in your hands, arms, legs or feet, and ringing in your ears.
  - Physical dependence is not the same as drug addiction. Your healthcare provider can tell you more about the differences between physical dependence and drug addiction.
  - Do not take more oxazepam than prescribed or take oxazepam for longer than prescribed.

What is oxazepam?

- Oxazepam is a prescription medicine used:
  - to treat anxiety disorders
  - for the short-term relief of the symptoms of anxiety or anxiety that can happen with depression
  - to treat anxiety, tension, agitation and irritability in elderly people
  - to relieve the symptoms of alcohol withdrawal including agitation, shakiness (tremor), anxiety associated with acute alcohol withdrawal.
- Oxazepam is a federal controlled substance (C-IV) because it contains oxazepam that can be abused or lead to dependence. Keep oxazepam capsules in a safe place to prevent misuse and abuse. Selling or giving away oxazepam capsules may harm others and is against the law. Tell your healthcare provider if you have abused or been dependent on alcohol, prescription medicines or street drugs.
- It is not known if oxazepam is safe and effective in children under 6 years of age.
- It is known if oxazepam is safe and effective for use longer than 4 months.

Do not take oxazepam capsules if you:

- are allergic to oxazepam or any of the ingredients in oxazepam capsules. See the end of this Medication Guide for a complete list of ingredients in oxazepam capsules.

Before you take oxazepam capsules, tell your healthcare provider about all of your medical conditions, including if you:

- have or have had depression, mood problems, or suicidal thoughts or behavior
- have liver or kidney problems
- have or have had problems with fainting or low blood pressure
- are pregnant or plan to become pregnant.
  - Taking oxazepam late in pregnancy may cause your baby to have symptoms of sedation (breathing problems, sluggishness, low muscle tone), and/or withdrawal symptoms (jitteriness, irritability, restlessness, shaking, excessive crying, feeding problems).
  - Tell your healthcare provider right away if you become pregnant or think you are pregnant during treatment with oxazepam.
- are breastfeeding or plan to breastfeed. Oxazepam may pass into your breast milk.
  - Breastfeeding during treatment with oxazepam may cause your baby to have sleepiness, feeding problems, and decreased weight gain.
  - Talk to your healthcare provider about the best way to feed your baby if you take oxazepam.

Tell your healthcare provider about all the medicines you take, including prescription and over-the-counter medicines, vitamins, and herbal supplements.

Taking oxazepam with certain other medicines can cause side effects or affect how well oxazepam or the other medicines work. Do not start or stop other medicines without talking to your healthcare provider.

How should I take oxazepam capsules?

• See “What is the most important information I should know about oxazepam?”

• Take oxazepam capsules exactly as your healthcare provider tells you to take it. Your healthcare provider will tell you how many oxazepam capsules to take and when to take them.

• If you take too many oxazepam capsules, call your healthcare provider or go to the nearest hospital emergency room right away.

What are the possible side effects of oxazepam?

Oxazepam may cause serious side effects, including:

- See “What is the most important information I should know about oxazepam?”
- Low blood pressure. Oxazepam can cause low blood pressure especially in elderly people.
- Oxazepam can make you sleepy or dizzy and can slow your thinking and motor skills.
  - Do not drive, operate heavy machinery, or do other dangerous activities until you know how oxazepam affects you.
  - Do not drink alcohol or take other drugs that may make you sleepy or dizzy while taking oxazepam without first talking to your healthcare provider. When taken with alcohol or drugs that cause sleepiness or dizziness, oxazepam may make your sleepiness or dizziness much worse.

The most common side effects of oxazepam include:

- drowsiness
- vertigo (sensation of loss of balance)
- dizziness
- headache

These are not all the possible side effects of oxazepam. Call your doctor for medical advice about side effects. You may report side effects to FDA at 1-800-FDA-1088.

How should I store oxazepam capsules?

- Store oxazepam capsules at room temperature between 68°F to 77°F (20°C to 25°C).
- Keep oxazepam capsules in a tightly closed container and out of the light.
- Keep oxazepam capsules and all medicines out of the reach of children.

General information about the safe and effective use of oxazepam capsules.

Medicines are sometimes prescribed for purposes other than those listed in a Medication Guide. Do not use oxazepam for a condition for which it was not prescribed. Do not give oxazepam capsules to other people, even if they have the same symptoms that you have. It may harm them. You can ask your pharmacist or healthcare provider for information about oxazepam that is written for health professionals.

What are the ingredients in oxazepam capsules?

Active ingredient: Oxazepam

Inactive ingredients: lactose monohydrate, pregelatinized starch, croscarmellose sodium, hypromellose, sodium lauryl sulfate, and magnesium stearate. The capsule shell contains gelatin and titanium dioxide. The 10 mg capsule also contains: D&C Red #28 and FD&C Red #40, the 15 mg capsule also contains: FD&C Red #40 and D&C Yellow #10 and the 30 mg capsule also contains: D&C Red #28, FD&C Red #40 and FD&C Blue #1. The imprinting ink contains strong ammonia solution, black iron oxide, potassium hydroxide, propylene glycol, purified water, titanium dioxide, FD&C Blue #2 aluminum lake and shellac.

Manufactured and Distributed by:

Leading Pharma, LLC
3 Oak road, Fairfield,
New Jersey (NJ) 07004
United States (USA)

This Medication Guide has been approved by the U.S. Food and Drug Administration Rev. 03 03/25

PACKAGE LABEL-PRINCIPAL DISPLAY PANEL - 10 mg (100 Capsules Bottle)

LEADING PHARMA
NDC 69315-911-01
Oxazepam capsules, USP 10 mg
Rx only
100 Capsules

LEADING PHARMA
NDC 69315-912-01
Oxazepam capsules, USP 15 mg
Rx only
100 Capsules

LEADING PHARMA
NDC 69315-913-01
Oxazepam capsules, USP 30 mg
Rx only
100 Capsules